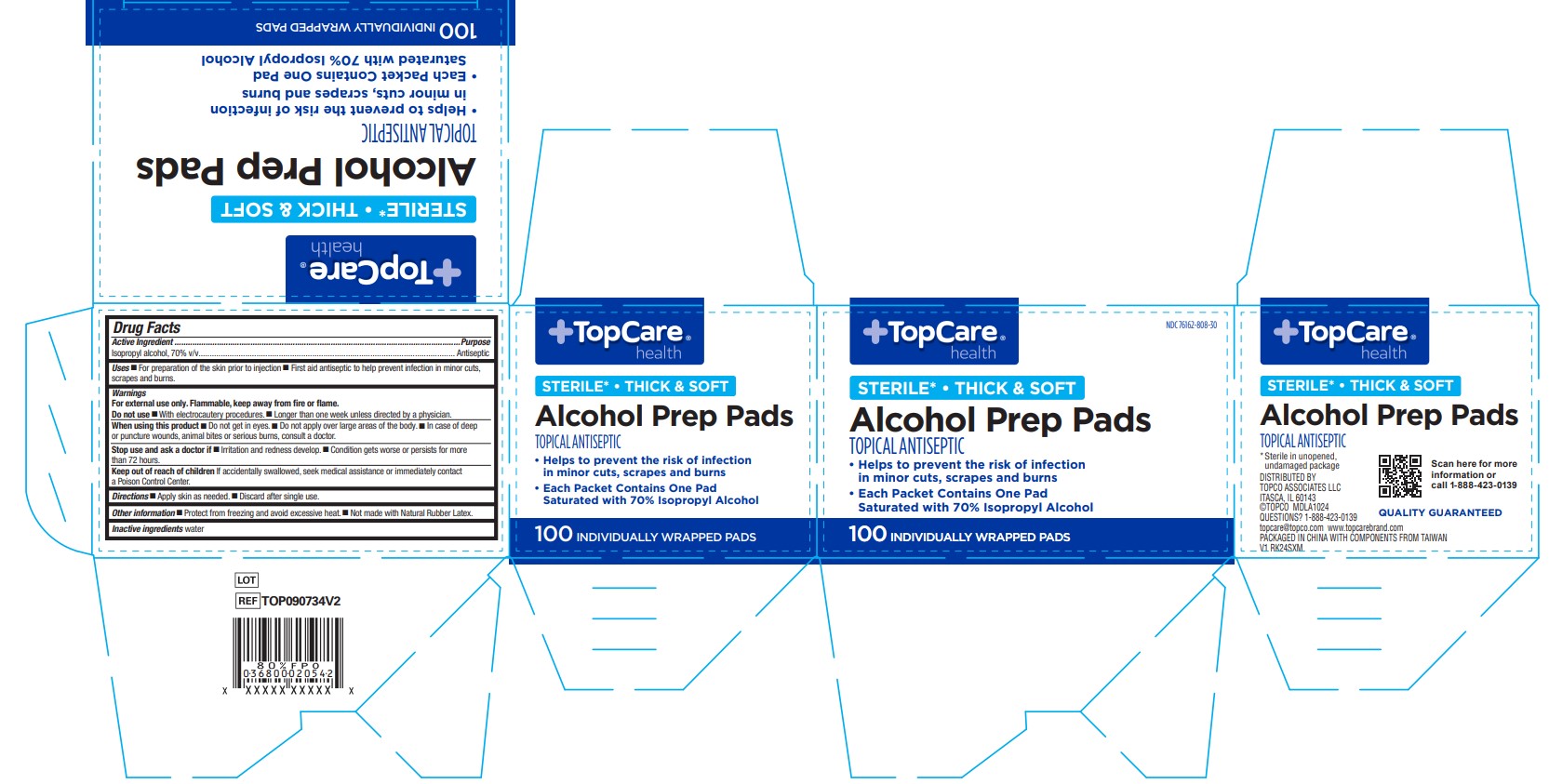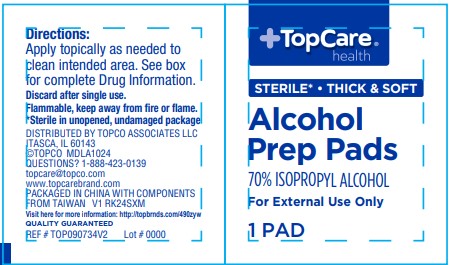 DRUG LABEL: Alcohol Prep Pads
NDC: 76162-808 | Form: SWAB
Manufacturer: Topco Associates
Category: otc | Type: HUMAN OTC DRUG LABEL
Date: 20250522

ACTIVE INGREDIENTS: ISOPROPYL ALCOHOL 70 mL/100 mL
INACTIVE INGREDIENTS: WATER

76162-808 TopCare IPA Prep Pads

Active Ingredient

Isopropyl alcohol, 70% v/v

Purpose

Antiseptic

Uses

- For preparation of the skin prior to injection
- First aid antiseptic to help prevent infection in minor cuts, scrapes and burns.

Warnings

For external use only. Flammable, keep away from fire or flame.

Do not use

- With electrocautery procedures.
- Longer than one week unless directed by a physician.

When using this product

- Do not get in eyes.
- Do not apply over large areas of the body.
- In case of deep or puncture wounds, animal bites or serious burns, consult a doctor.

Stop use and ask a doctor if

- Irritation and redness develop.
- Condition gets worse or persists for more than 72 hours.

Keep out of reach of children

If accidentally swallowed, seek medical assistance or immediately contact a Poison Control Center.

Directions

- Apply to skin as needed.
- Discard after single use.

Other information

- Protect from freezing and avoid excessive heat.
- Not made with Natural Rubber Latex.

Inactive ingredients

water

Manufacturer information

DISTRIBUTED BY TOPCO ASSOCIATES LLC

ITASCA, IL 60143

©TOPCO MDLA1024

QUESTIONS? 1-888-423-0139

topcare@topco.com www.topcarebrand.com

PACKAGED IN CHINA WITH COMPONENTS FROM TAIWAN

REF TOP090734V2 V1 RK24SXM